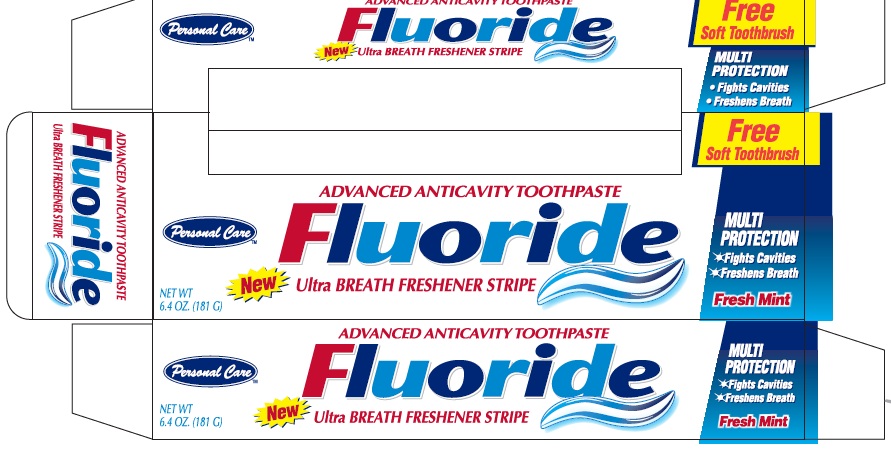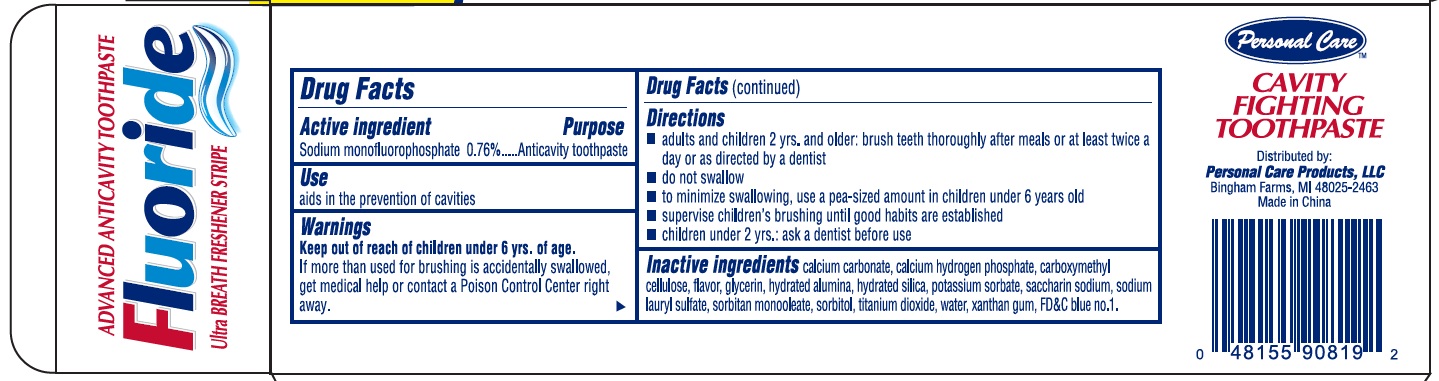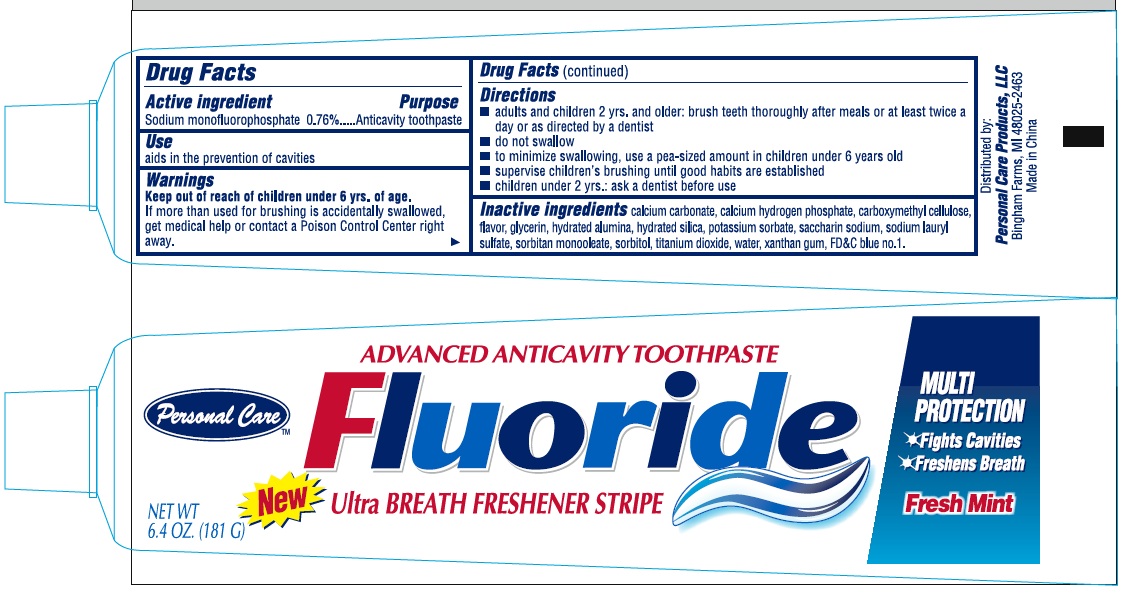 DRUG LABEL: ADVANCED FLUORIDE ANTICAVITY
NDC: 29500-9181 | Form: PASTE, DENTIFRICE
Manufacturer: Personal Care Products, LLC
Category: otc | Type: HUMAN OTC DRUG LABEL
Date: 20170801

ACTIVE INGREDIENTS: SODIUM MONOFLUOROPHOSPHATE 1000 mg/181 g
INACTIVE INGREDIENTS: CALCIUM CARBONATE; ANHYDROUS DIBASIC CALCIUM PHOSPHATE; POWDERED CELLULOSE; GLYCERIN; ALUMINUM OXIDE; HYDRATED SILICA; POTASSIUM SORBATE; SACCHARIN SODIUM; SODIUM LAURYL SULFATE; SORBITAN MONOOLEATE; SORBITOL; TITANIUM DIOXIDE; WATER; XANTHAN GUM; FD&C BLUE NO. 1

ADVANCED FLUORIDE ANTICAVITY TOOTHPASTE - 9181

Active Ingredient Drug Facts

Sodium Monofluorophosphate 0.76%

Purpose

Anticavity toothpaste

Use

Aids in the prevention of cavities

Warnings

If more than is used for brushing is accidentally swallowed get medical help or contact a poison control center right away.

Keep out of reach of children under 6 yrs of age.

Directions

adults and children 2 years. and older: brush teeth thoroughly after meals or at least twice a day or as directed by a dentist.

do not swallow

to minimize swallowing, use a pea-sized amount in children under 6 years old

supervise children's brushing until good habits are established

children under 2y ears: ask a dentist before use.

inactive ingredients

calcium carbonate, calcium hydrogen phosphate, carboxymethyl cellulose, flavor, glycerin, hydrated alumina, hydrated silica, potassium sorbate, saccharin sodium, sodium lauryl sulfate, sorbitan monooleate, sorbitol, titanium dioxide, water, xanthan gum.

ADVANCED FLUORIDE ANTICAVITY product label

CAVITY FIGHTING TOOTHPASTE

Distributed by:

Personal Care Products, LLC

Bingham Farms, MI 48025-2463

Made in China

Advanced Fluoride Anticavity Toothpaste

New Ultra Breath Freshener Stripe

Net Wt 6.4oz (181g)

Multi
Protection

Fights Cavities

Freshens Breath